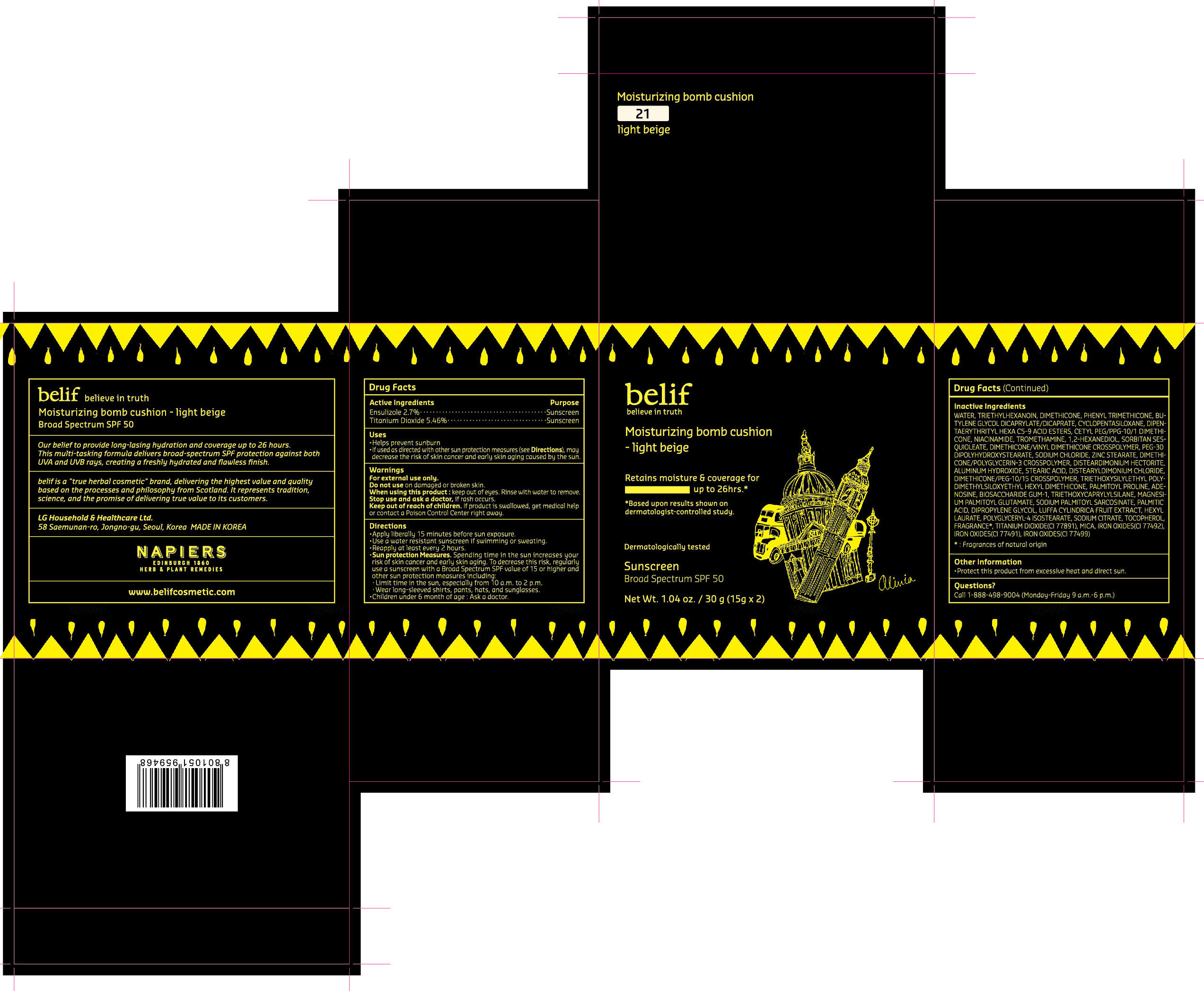 DRUG LABEL: belif Moisturizing bomb cushion compact - light beige
NDC: 53208-700 | Form: POWDER
Manufacturer: LG Household and Health Care Inc
Category: otc | Type: HUMAN OTC DRUG LABEL
Date: 20170101

ACTIVE INGREDIENTS: TITANIUM DIOXIDE 0.819 g/15 g; ENSULIZOLE 0.405 g/15 g
INACTIVE INGREDIENTS: DISTEARDIMONIUM HECTORITE; SODIUM CHLORIDE; WATER; DIPROPYLENE GLYCOL; NIACINAMIDE; TROMETHAMINE; 1,2-HEXANEDIOL; STEARIC ACID; ALUMINUM HYDROXIDE; SORBITAN SESQUIOLEATE; DIMETHICONE/VINYL DIMETHICONE CROSSPOLYMER (SOFT PARTICLE); BIOSACCHARIDE GUM-1; PHENYL TRIMETHICONE; SODIUM CITRATE; SODIUM PALMITOYL SARCOSINATE; PALMITOYL PROLINE; PEG-30 DIPOLYHYDROXYSTEARATE; MAGNESIUM PALMITOYL GLUTAMATE; DISTEARYLDIMONIUM CHLORIDE; PALMITIC ACID; TOCOPHEROL; TRIETHOXYCAPRYLYLSILANE; TRIETHYLHEXANOIN; ZINC STEARATE; PHENOXYETHANOL; POLYGLYCERYL-4 ISOSTEARATE; LUFFA AEGYPTIACA FRUIT; CETYL PEG/PPG-10/1 DIMETHICONE (HLB 2); HEXYL LAURATE; BUTYLENE GLYCOL DICAPRYLATE/DICAPRATE; ADENOSINE; CYCLOMETHICONE 5; DIMETHICONE; DIPENTAERYTHRITYL HEXA C5-9 ACID ESTERS

ACTIVE INGREDIENTS

ENSULIZOLE 2.7%, TITANIUM DIOXIDE 5.46%

PURPOSE

Sunscreen

USES

- Helps prevent sunburn.
- If used as directed with other sun protection measures (see Directions), may decrease the risk of skin cancer and early skin aging caused by the sun.

WARNINGS

For external use only

Do not use on damaged or broken skin.

When using this product: Keep out of the eyes. Rinse with water to remove.

Stop use and ask doctor, if rash occurs.

Keep out of reach of children. If product is swallowed, get medical help or

contact a Posion Control Center right away.

DIRECTIONS

- Apply liberally 15 minutes before sun exposure.
- Use a water resistant sunscreen if swimming or sweating.
- Reapply at least every 2 hours.
- Sun Protection Measures. Spending time in the sun increases your risk of skin cancer and early skin aging. To decrease this risk, regularly use a sunscreen with a Broad Spectrum SPF value of 15 or higher and othersun protection measures including:

- Limit time in the sun, especially from 10 a.m. to 2 p.m.

- Wear longsleeved shirts, pants, hats, and sunglasses.

- Children under 6 months: Ask a doctor.

OTHER INFORMATION

- Protect the product in this container from excessive heat and direct sun.

INACTIVE INGREDIENTS

WATER, TRIETHYLHEXANOIN, DIMETHICONE, PHENYL TRIMETHICONE, BUTYLENE GLYCOL DICAPRYLATE/DICAPRATE, CYCLOPENTASILOXANE, DIPENTAERYTHRITYL HEXA C5-9 ACID ESTERS, CETYL PEG/PPG-10/1 DIMETHICONE, NIACINAMIDE, TROMETHAMINE, 1,2-HEXANEDIOL, SORBITAN SESQUIOLEATE, DIMETHICONE/VINYL DIMETHICONE CROSSPOLYMER, PEG-30 DIPOLYHYDROXYSTEARATE, SODIUM CHLORIDE, ZINC STEARATE, DIMETHICONE/POLYGLYCERIN-3 CROSSPOLYMER, DISTEARDIMONIUM HECTORITE, ALUMINUM HYDROXIDE, STEARIC ACID, DISTEARYLDIMONIUM CHLORIDE, DIMETHICONE/PEG-10/15 CROSSPOLYMER, TRIETHOXYSILYLETHYL, POLYDIMETHYLSILOXYETHYL HEXYL DIMETHICONE, PALMITOYL PROLINE, ADENOSINE, BIOSACCHARIDE GUM-1, TRIETHOXYCAPRYLYLSILANE, MAGNESIUM PALMITOYL GLUTAMATE, SODIUM PALMITOYL SARCOSINATE, PALMITIC ACID, DIPROPYLENE GLYCOL, LUFFA CYLINDRICA FRUIT EXTRACT, HEXYL LAURATE, POLYGLYCERYL-4 ISOSTEARATE, SODIUM CITRATE, TOCOPHEROL, FRAGRANCE*, TITANIUM DIOXIDE(CI 77891), MICA, IRON OXIDES(CI 77492), IRON OXIDES(CI 77491), IRON OXIDES(CI 77499)

PRINCIPAL DISPLAY PANEL - 30 g (15 g x 2) Light Beige

belif

Moisturizing bomb cushion compact - light beige

Provides moisture & coverage for up to 26 hrs.*

Dermatologically tested

Sunscreen Broad Spectrum SPF 50

Net Wt. 1.04 oz / 30 g (15g x 2)